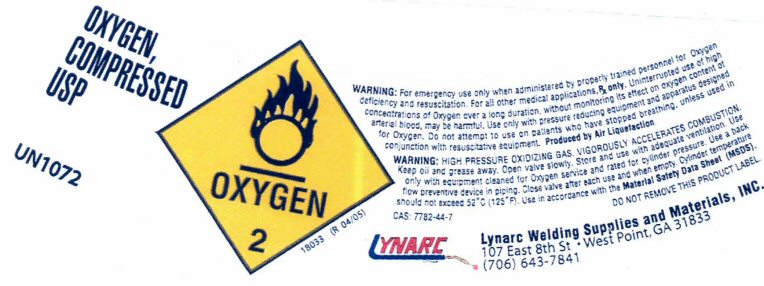 DRUG LABEL: OXYGEN
NDC: 58166-001 | Form: GAS
Manufacturer: Lynarc Welding Supplies & Material, Inc.
Category: prescription | Type: HUMAN PRESCRIPTION DRUG LABEL
Date: 20241028

ACTIVE INGREDIENTS: OXYGEN 99 L/100 L

OXYGEN COMPRESSED USP UN1072 OXYGEN 2 18033 (R 04/05)
WARNING: For emergency use only when administered by properly trained personnel for Oxygen deficiency and resuscitation. For all other medical applications, Rx only. Uninterrupted use of high concentrations of Oxygen over a long duration, without monitoring its effect on oxygen content of arterial blood, may be harmful. Use only with pressure reducing equipment and apparatus designed for Oxygen. Do not attempt to use on patients who have stopped breathing, unless used in conjunction with resuscitative equipment. Produced by Air Liquefaction.
WARNING:HIGH PRESSURE OXIDIZING GAS. VIGOROUSLY ACCELERATES COMBUSTION. Keep oil and grease away. Open valve slowly. Store and use with adequate ventilation. Use only with equipment cleaned for Oxygen service and rated for cylinder pressure. Use a back flow preventive device in the piping. Close valve after each use and when empty. Cylinder temperature should not exceed 52 degrees C (125 degrees F). Use in accordance with the Material Safety Data Sheet (MSDS).
CAS: 7782-44-7 DO NOT REMOVE THIS PRODUCT LABEL

Lynarc Welding Supplies and Materials, Inc.

107 East 8th St. West Point, GA 31833 (706) 643-7841